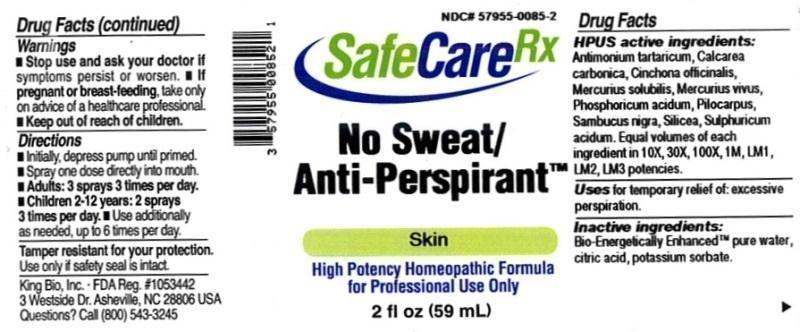 DRUG LABEL: No Sweat Anti-Perspirant
NDC: 57955-0085 | Form: LIQUID
Manufacturer: King Bio Inc.
Category: homeopathic | Type: HUMAN OTC DRUG LABEL
Date: 20150319

ACTIVE INGREDIENTS: ANTIMONY POTASSIUM TARTRATE 10 [hp_X]/59 mL; OYSTER SHELL CALCIUM CARBONATE, CRUDE 10 [hp_X]/59 mL; CINCHONA OFFICINALIS BARK 10 [hp_X]/59 mL; MERCURIUS SOLUBILIS 10 [hp_X]/59 mL; MERCURY 10 [hp_X]/59 mL; PILOCARPUS JABORANDI LEAF 10 [hp_X]/59 mL; PHOSPHORIC ACID 10 [hp_X]/59 mL; SAMBUCUS NIGRA FLOWERING TOP 10 [hp_X]/59 mL; SILICON DIOXIDE 10 [hp_X]/59 mL; SULFURIC ACID 10 [hp_X]/59 mL
INACTIVE INGREDIENTS: WATER; ANHYDROUS CITRIC ACID; POTASSIUM SORBATE

No Sweat Anti-Perspirant™

ACTIVE INGREDIENT

Drug Facts__________________________________________________________________________________________________________

HPUS active ingredients: Antimonium tartaricum, Calcarea carbonica, Cinchona officinalis, Mercurius solubilis, Mercurius vivus, Pilocarpus, Phosphoricum acidum, Sambucus nigra, Silicea, Sulphuricum acidum. Equal volumes of each ingredient in 10X, 30X, 100X, 1M, LM1, LM2, LM3 potencies.

INDICATIONS AND USAGE

Uses for temporary relief of: excessive perspiration.

Inactive Ingredients:

Bio-Energetically Enhanced™ pure water, citric acid and potassium sorbate.

Warnings

- Stop use and ask your doctor if symptoms persist or worsen.
- If pregnant or breast-feeding, take only on advice of a healthcare professional.

- Keep out of reach of children.

Directions

- Initially, depress pump until primed.
- Spray one dose directly into mouth.
- Adults: 3 sprays 3 times per day.
- Children 2-12: 2 sprays 3 times per day.
- Use additionally as needed, up to 6 times per day.

OTHER SAFETY INFORMATION

Tamper resistant for your protection. Use only if safety seal is intact. This product has not been independently tested.

PURPOSE

Uses for temporary relief of:

- excessive perspiration.